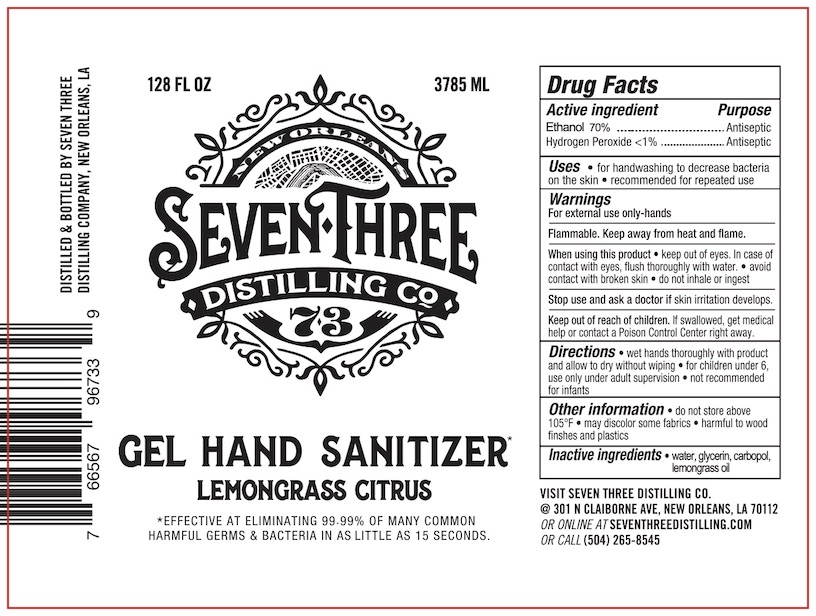 DRUG LABEL: Seven Three Hand Sanitizer
NDC: 75219-7300 | Form: GEL
Manufacturer: Seven Three Distilling Company, LLC
Category: otc | Type: HUMAN OTC DRUG LABEL
Date: 20210209

ACTIVE INGREDIENTS: HYDROGEN PEROXIDE 0.125 mL/100 mL; ALCOHOL 70 mL/100 mL
INACTIVE INGREDIENTS: WEST INDIAN LEMONGRASS OIL 0.002 mL/100 mL; METHACRYLIC ACID - ETHYL ACRYLATE COPOLYMER (4500 MPA.S) 5.5 mL/100 mL; GLYCERIN 1.45 mL/100 mL; WATER

This is a hand sanitizer manufactured according to the Temporary Policy for Preparation of Certain Alcohol-Based Hand Sanitizer Products During the Public Health Emergency (CoViD-19); Guidance for Industry.

The hand sanitizer is manufactured using only the following United States Pharmacopoeia (USP) grade ingredients in the preparation of the product (percentage in final product formulation) consistent with World Health Organization (WHO) recommendations:

1. Alcohol (ethanol) (USP or Food Chemical Codex (FCC) grade) (70%, volume/volume (v/v)) in an aqueous solution denatured according to Alcohol and Tobacco Tax and Trade Bureau regulations in 27 CFR part 20.
2. Glycerol (1.45% v/v).
3. Hydrogen peroxide (0.125% v/v).
4. Sterile distilled water or boiled cold water.
5. Methacrylic Acid - Ethyl Acrylate Copolymer (5.5% v/v)

The firm does add other active or inactive ingredients. Different or additional ingredients may impact the quality and potency of the product.

Active Ingredient(s)

Ethanol 70%. Purpose: Antiseptic

Hydrogen Peroxide <1%. Purpose: Antiseptic

Use

- For handwashing to decrease bacteria on the skin
- recommended for repeated use

Warnings

For external use only - hands.

Flammable. Keep away from heat or flame.

When usting this product keep out of eyes. In case of contact with eyes, flush thoroughly with water. Avoid contact with broken skin. Do not inhale or ingest.

Stop use and ask a doctor if skin irritation develops.

Keep out of reach of children. If swallowed, get medical help or contact a Poison Control Center right away.

Warnings

- for children under 6, use only under adult supervision
- not recommended for infants
- avoid contact with broken skin

When using this product keep out of eyes. In case of contact with eyes, flush thoroghly with water.

Avoid contact with broken skin.

Do not ingest or inhale.

Stop use and ask a doctor if skin irritation develops.

Keep out of reach of children. If swallowed, get medical help or help or contact a Poison Control Center right away.

Stop use and ask a doctor if skin irritation develops.

Keep out of reach of children. If swallowed, get medical help or contact a Poison Control Center right away.

Directions

- Wet hands thoroughly with product and allow to dry without wiping.
- For childres under 6, use only under adult supervision
- Not recommended for infants

Other information

- Do not store above 105°F
- May discolor some fabrics
- harmful to wood finishes and plastics

Inactive ingredients

water, glycerin, carbopol, lemongrass oil

Purpose

Antiseptic, Hand Sanitizer

Package Label - Principal Display Panel

128 FL OZ (3785ML) 75219-7300-1